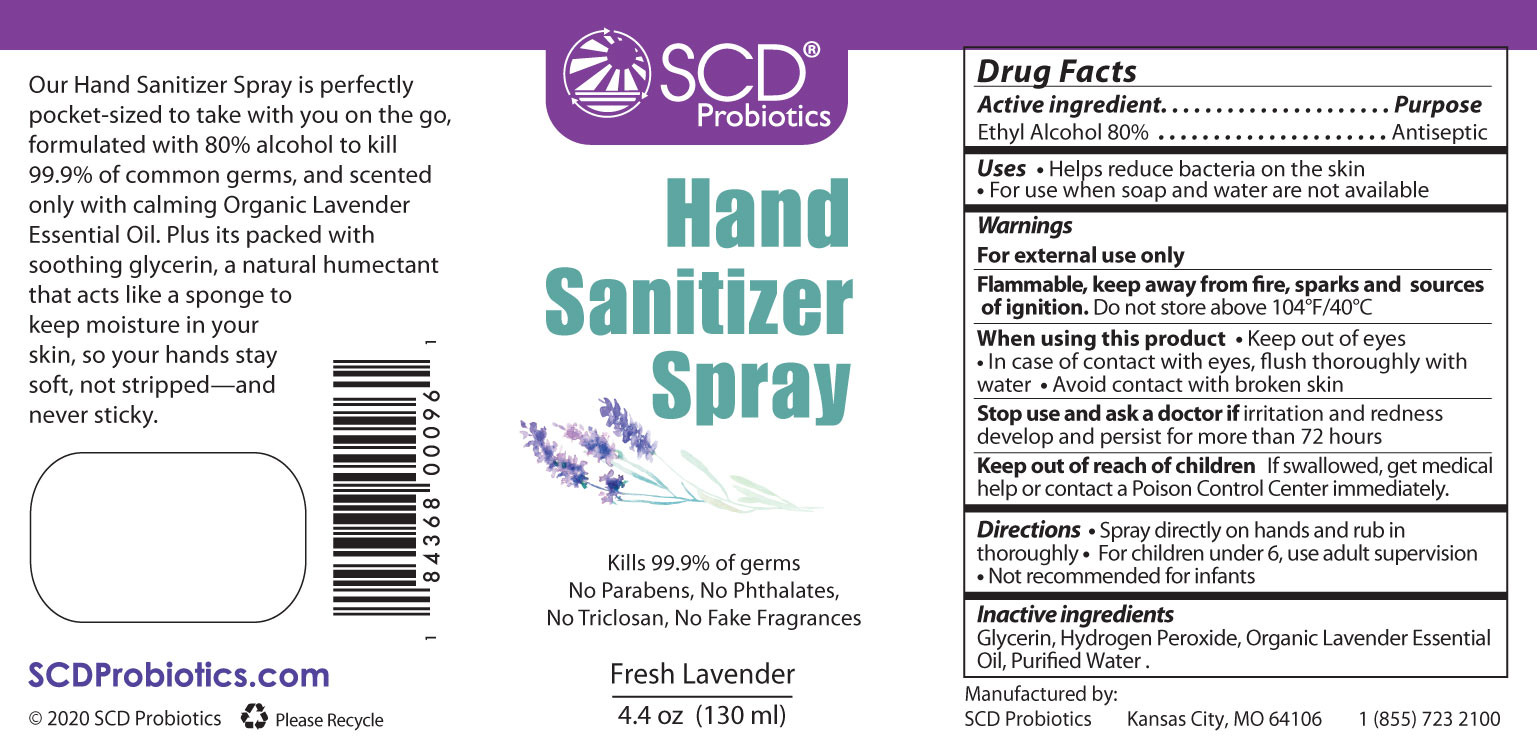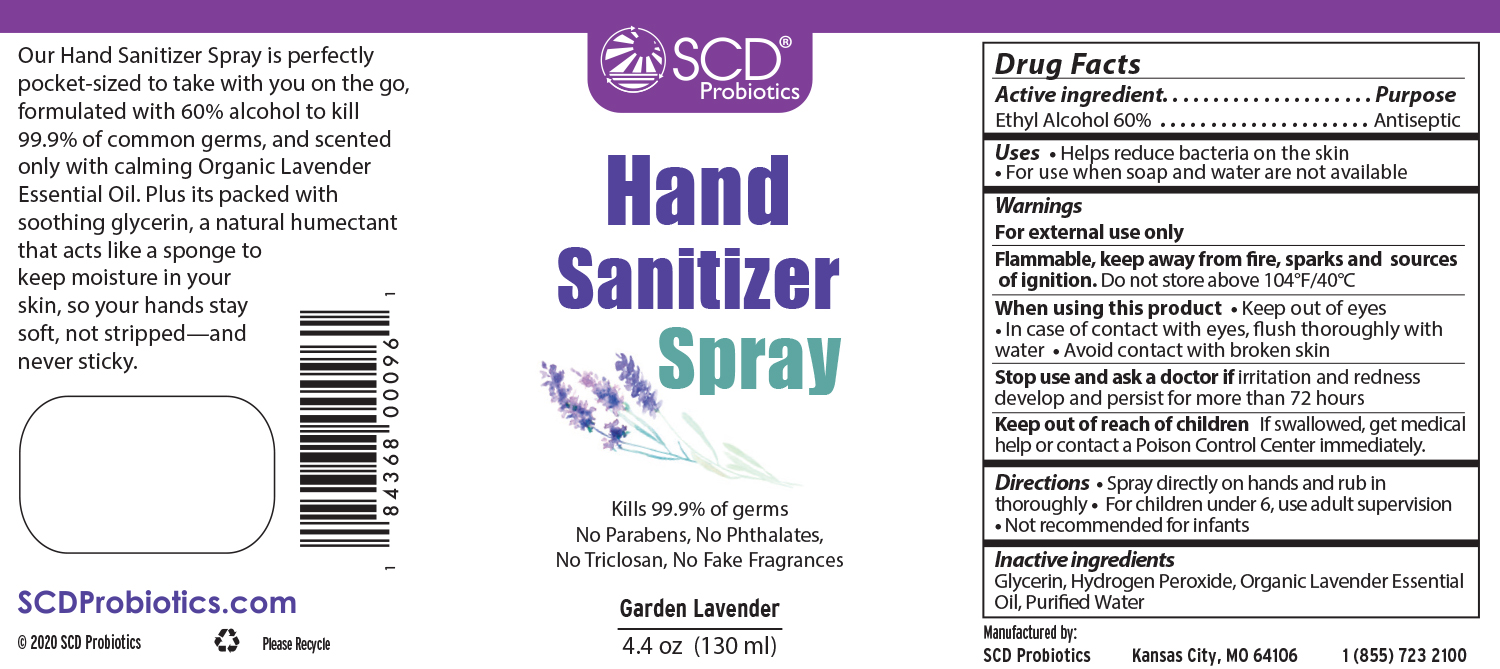 DRUG LABEL: Hand Sanitizer 60% LV
NDC: 79107-323 | Form: LIQUID
Manufacturer: Sustainable Community Development, L.L.C.
Category: otc | Type: HUMAN OTC DRUG LABEL
Date: 20210107

ACTIVE INGREDIENTS: ALCOHOL 60 mL/100 mL
INACTIVE INGREDIENTS: WATER 31.02 mL/100 mL; GLYCERIN 1.45 mL/100 mL; LAVENDER OIL 0.4 mL/100 mL; HYDROGEN PEROXIDE 0.13 mL/100 mL

Hand Sanitizer version 3.0 submission Lavender

Active Ingredient - 80% Ethyl Alcohol

PURPOSE

Uses: Helps reduce bacteria on the skin.

For use when soap and water are not available.

WARNINGS

For external use only.

When using this product:

Keep out of eyes.

In case of contact with eyes, flush thoroughly with water.

Avoid contact with broken skin

Stop use and call a doctor if irritation and redness develop and persist for more than 72 hours

Keep out of reach of children. If swallowed, get medical help or contact a Poison Control Center immediately.

DOSAGE AND ADMINISTRATION

Spray directly on hands and rub in thoroughly. For children under 6, use adult supervision. Not recommended for infants.

INACTIVE INGREDIENT

Glycerin, Hydrogen Peroxide, Organic Lavender Essential Oil, Purified Water

INDICATIONS AND USAGE

Uses: Helps reduce bacteria on the skin. For use when soap and water are not available.

PACKAGE LABEL

130 mL NDC 79107-321-44